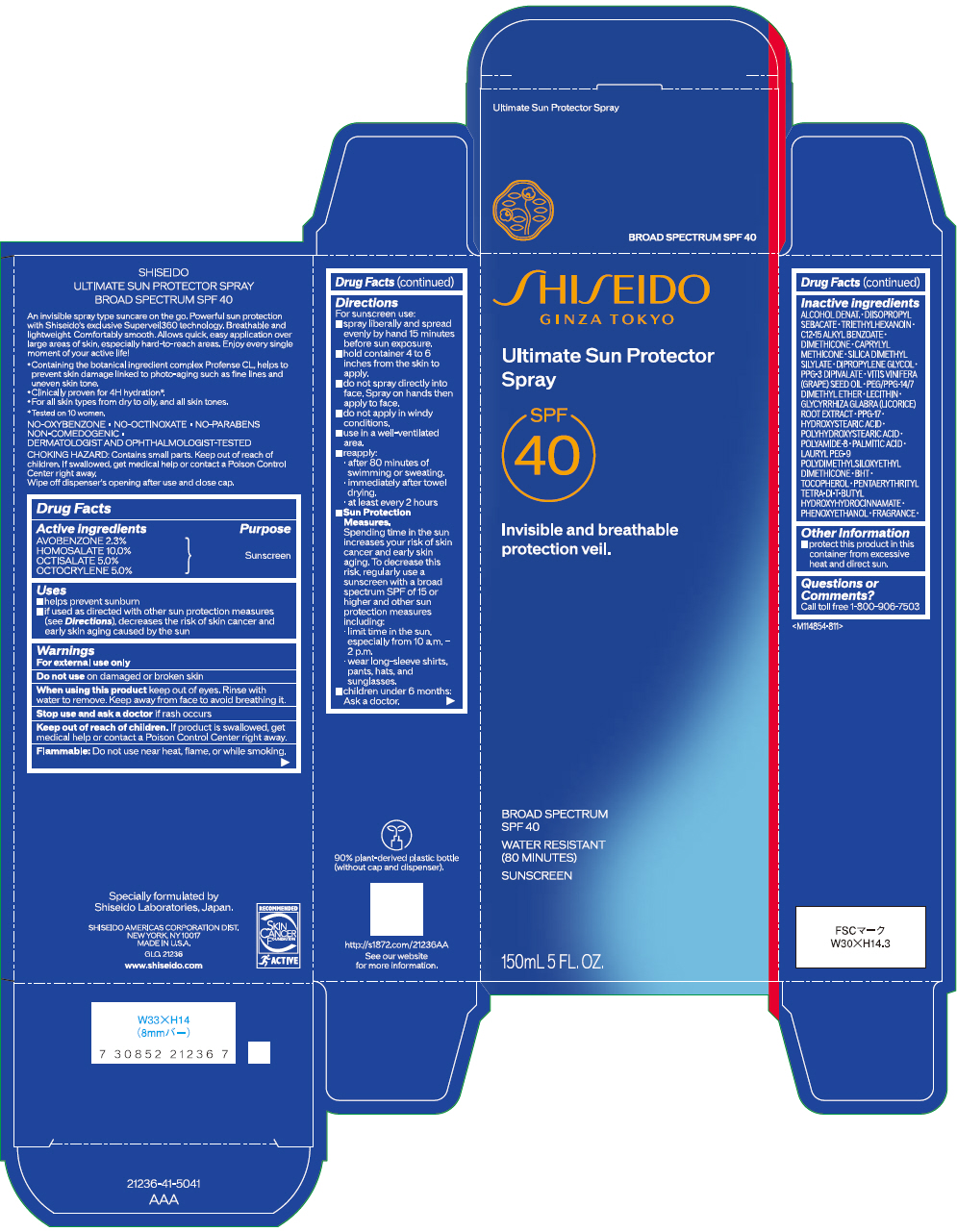 DRUG LABEL: SHISEIDO ULTIMATE SUN PROTECTOR
NDC: 58411-891 | Form: SPRAY
Manufacturer: SHISEIDO AMERICAS CORPORATION
Category: otc | Type: HUMAN OTC DRUG LABEL
Date: 20260106

ACTIVE INGREDIENTS: AVOBENZONE 3.1533 g/150 mL; HOMOSALATE 13.71 g/150 mL; OCTISALATE 6.855 g/150 mL; OCTOCRYLENE 6.855 g/150 mL
INACTIVE INGREDIENTS: ALCOHOL; DIISOPROPYL SEBACATE; TRIETHYLHEXANOIN; ALKYL (C12-15) BENZOATE; DIMETHICONE; CAPRYLYL TRISILOXANE; SILICA DIMETHYL SILYLATE; DIPROPYLENE GLYCOL; GRAPE SEED OIL; PEG/PPG-14/7 DIMETHYL ETHER; LECITHIN, SOYBEAN; GLYCYRRHIZA GLABRA; PPG-17; 12-HYDROXYSTEARIC ACID; POLYHYDROXYSTEARIC ACID (2300 MW); POLYAMIDE-8 (4500 MW); PALMITIC ACID; LAURYL PEG-9 POLYDIMETHYLSILOXYETHYL DIMETHICONE; BUTYLATED HYDROXYTOLUENE; .ALPHA.-TOCOPHEROL; PENTAERYTHRITOL TETRAKIS(3-(3,5-DI-TERT-BUTYL-4-HYDROXYPHENYL)PROPIONATE); PHENOXYETHANOL

SHISEIDO ULTIMATE SUN PROTECTOR SPRAY

Drug Facts

ACTIVE INGREDIENT

Active ingredients | Purpose
AVOBENZONE 2.3% | Sunscreen
HOMOSALATE 10.0% | Sunscreen
OCTISALATE 5.0% | Sunscreen
OCTOCRYLENE 5.0% | Sunscreen

Uses

- helps prevent sunburn
- if used as directed with other sun protection measures (see Directions), decreases the risk of skin cancer and early skin aging caused by the sun

Warnings

For external use only

Do not useon damaged or broken skin

WHEN USING

When using this productkeep out of eyes. Rinse with water to remove.

Stop use and ask a doctorif rash occurs.

Keep out of reach of children.If product is swallowed, get medical help or contact a Poison Control Center right away.

Flammable

Do not use near heat, flame, or while smoking

Directions

For sunscreen use:

- spray liberally and spread evenly by hand 15 minutes before sun exposure
- hold container 4 to 6 inches from the skin to apply.
- do not spray directly into face. Spray on hands then apply to face.
- do not apply in windy conditions.
- use in a well-ventilated area.
- reapply:
  - after 80 minutes of swimming or sweating
  - immediately after towel drying.
  - at least every 2 hours
- Sun Protection Measures. Spending time in the sun increases your risk of skin cancer and early skin aging. To decrease this risk, regularly use a sunscreen with a broad spectrum SPF of 15 or higher and other sun protection measures including:
  - limit time in the sun, especially from 10 a.m. – 2 p.m.
  - wear long-sleeve shirts, pants, hats, and sunglasses
- children under 6 months: Ask a doctor

Inactive Ingredients

ALCOHOL DENAT.•DIISOPROPYL SEBACATE•TRIETHYLHEXANOIN•C12-15 ALKYL BENZOATE•DIMETHICONE•CAPRYLYL METHICONE•SILICA DIMETHYL SILYLATE•DIPROPYLENE GLYCOL•PPG-3 DIPIVALATE•VITIS VINIFERA (GRAPE) SEED OIL•PEG/PPG-14/7 DIMETHYL ETHER•LECITHIN•GLYCYRRHIZA GLABRA (LICORICE) ROOT EXTRACT•PPG-17•HYDROXYSTEARIC ACID•POLYHYDROXYSTEARIC ACID•POLYAMIDE-8•PALMITIC ACID•LAURYL PEG-9 POLYDIMETHYLSILOXYETHYL DIMETHICONE•BHT•TOCOPHEROL•PENTAERYTHRITYL TETRA-DI-T-BUTYL HYDROXYHYDROCINNAMATE•PHENOXYETHANOL•FRAGRANCE•

Other information

- protect this product in this container from excessive heat and direct sun.

Questions or comments?

Call toll free 1-800-906-7503

PRINCIPAL DISPLAY PANEL - 150 mL Cartridge Carton

SHISEIDO
GINZA TOKYO

Ultimate Sun Protector
Spray

SPF
40

Invisible and breathable
protection veil.

BROAD SPECTRUM
SPF 40

WATER RESISTANT
(80 MINUTES)

SUNSCREEN

150mL 5 FL. OZ.